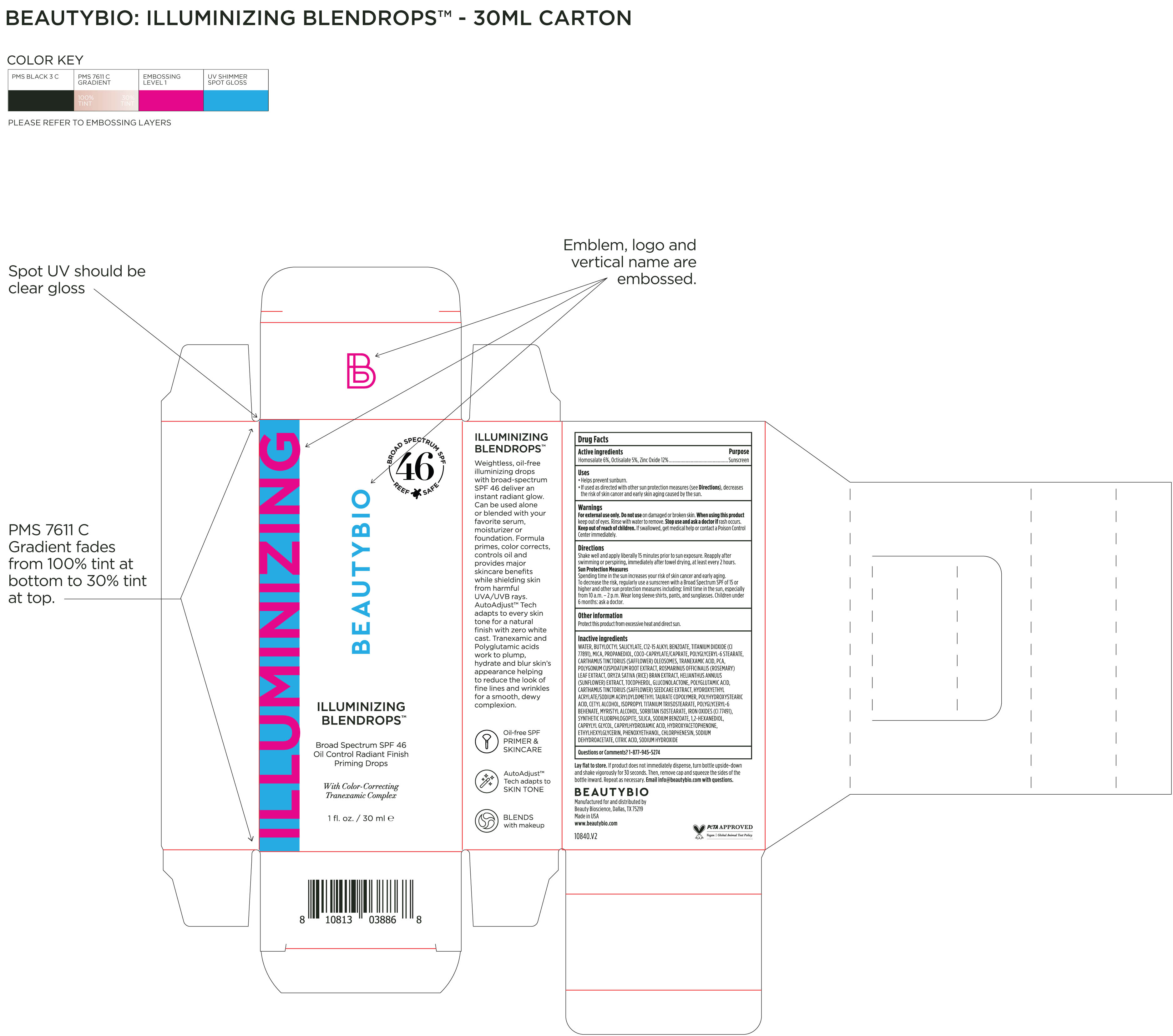 DRUG LABEL: Illuminizing Blendrops Broad Spectrum SPF 46
NDC: 44717-088 | Form: SOLUTION/ DROPS
Manufacturer: Wasatch Product Development, LLC
Category: otc | Type: HUMAN OTC DRUG LABEL
Date: 20251118

ACTIVE INGREDIENTS: HOMOSALATE 6 g/100 mL; OCTISALATE 5 g/100 mL; ZINC OXIDE 12 g/100 mL
INACTIVE INGREDIENTS: CARTHAMUS TINCTORIUS (SAFFLOWER) OLEOSOMES; ROSEMARY; GLUCONOLACTONE; 1,2-HEXANEDIOL; CHLORPHENESIN; SORBITAN ISOSTEARATE; CAPRYLYL GLYCOL; HYDROXYACETOPHENONE; PCA; WATER; BUTYLOCTYL SALICYLATE; COCO-CAPRYLATE/CAPRATE; TOCOPHEROL; CETYL ALCOHOL; TRANEXAMIC ACID; HELIANTHUS ANNUUS FLOWERING TOP; MAGNESIUM POTASSIUM ALUMINOSILICATE FLUORIDE; PHENOXYETHANOL; MYRISTYL ALCOHOL; CARTHAMUS TINCTORIUS SEEDCAKE; SILICA; SODIUM BENZOATE; SODIUM DEHYDROACETATE; SODIUM HYDROXIDE; CI 77491; ETHYLHEXYLGLYCERIN; POLYHYDROXYSTEARIC ACID (2300 MW); TITANIUM DIOXIDE; POLYGLUTAMIC ACID (1200 MW); HYDROXYETHYL ACRYLATE/SODIUM ACRYLOYLDIMETHYL TAURATE COPOLYMER (45000 MPA.S AT 1%); ISOPROPYL TITANIUM TRIISOSTEARATE; PROPANEDIOL; CAPRYLHYDROXAMIC ACID; CITRIC ACID; C12-15 ALKYL BENZOATE; MICA; POLYGLYCERYL-6 STEARATE; ORYZA SATIVA (RICE) BRAN; POLYGONUM CUSPIDATUM ROOT; POLYGLYCERYL-6 BEHENATE

Illuminizing Blendrops Broad Spectrum SPF 46

Drug Facts

Active ingredients Puropse

Homosalate 6%.... Sunscreen

Octisalate 5%

Zinc Oxide 12%

Uses

- Helps prevent sunburn.
- If used as directed with other sun protection measures (see Directions), decreases the risk of skin cancer and early skin aging casued by the sun.

- Keep out of reach of children. If swallowed, get medical help or contact a Poison Control Center immediately.

Stop use and ask a doctor if rash occurs.

WARNINGS

For external use only. Do not use on damaged or broken skin. When using this product keep out of eyes. Rinse with water to remove.

Directions

Shake well and apply liberally 15 minutes prior to sun exposure. Reapply after swimming or perspiring, immediately after towel drying, at least every 2 hours.

Sun Protection Measures

Spending time in the sun increases your risk of skin cancer and early aging. To decrease the risk, regularyl use a sunscreen with a Broad Spectrum SPF of 15 or higher and other sun protection measures including: limit time in the sun, especially from 10 a.m.- 2p.m. Wear long sleeves shirts, pants, and sunglasses. Children under 6 months: ask a doctor.

Inactive ingredients

Water, Butyloctyl Salicylate, C12-15 Alkyl Benzoate. Titanium Dioxide (CI 77891), Mica, Propanediol, Coco-Caprylate/Caprate, Polyglyceryl-6 Stearate, Carthamus Tinctorius (Safflower) Oleosomes, Tranexamic Acid, PCA, Polygonum Cuspidatum Root Extract, Rosmarinus Officinalis (Rosemary) Leaf Extract, Oryza Sativa (Rice) Bran Extract, Helianthus Annuus (Sunflower) Extract, Tocopherol, Gluconolactone, Polyglytamic Acid, Carthamus Tinctorius (Safflower) Seedcake Extract, Hydroxyethyl Acryleta/Sodium Acryloyldimethyl Taurate Copolymer, Polyhydroxystearic Acid, Cetyl Alcohol, Isopropryl Titanium Triisostearate, Iron Oxides (CI 77491), Synthetic Fluorphlogopite, Silica, Sodium Benzoate, 1,2-Hexanediol, Caprylyl Glycol, Caprylhydroxamic Acid, Hydroxyacetophenone, Ethylhexylglycerin, Phenoxyethanol, Chlorphenesin, Sodium Dehydroacetate, Citric Acid, Sodium Hydroxide.

PACKAGE LABEL

ILLUMINIZING BLENDROPS

Broad Spectrum SPF 46

Oil Control Radiant Finish Priming Drops

With Color-Correcting Tranexamic Complex

1 fl. oz. /30 ml